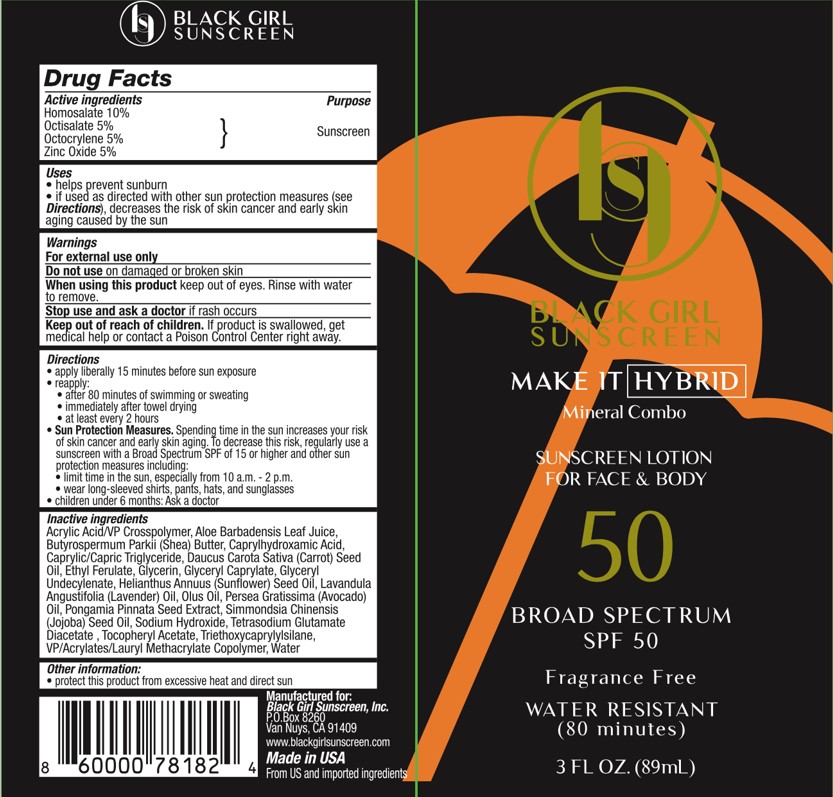 DRUG LABEL: Black Girl Sunscreen
NDC: 84204-0002 | Form: LOTION
Manufacturer: Black Girl Sunscreen, LLC
Category: otc | Type: HUMAN OTC DRUG LABEL
Date: 20250115

ACTIVE INGREDIENTS: OCTOCRYLENE 50 mg/1 mL; ZINC OXIDE 50 mg/1 mL; HOMOSALATE 100 mg/1 mL; OCTISALATE 50 mg/1 mL
INACTIVE INGREDIENTS: GLYCERYL CAPRYLATE; CORN OIL; TRIETHOXYCAPRYLYLSILANE; MEDIUM-CHAIN TRIGLYCERIDES; LAVENDER OIL; ETHYL FERULATE; GLYCERYL 1-UNDECYLENATE; MILLETTIA PINNATA SEED; CAPRYLHYDROXAMIC ACID; GLYCERIN; ALOE VERA LEAF; EDETATE DISODIUM; AVOCADO OIL; CARROT SEED OIL; WATER; SUNFLOWER SEED; JOJOBA OIL; .ALPHA.-TOCOPHEROL ACETATE; SODIUM HYDROXIDE; SHEA BUTTER; BUTYL ACRYLATE/C16-C20 ALKYL METHACRYLATE/METHACRYLIC ACID/METHYL METHACRYLATE COPOLYMER; CARBOMER INTERPOLYMER TYPE A (ALLYL SUCROSE CROSSLINKED); TETRASODIUM GLUTAMATE DIACETATE

Black Girl Mineral Combo Sunscreen Lotion for Face & Body Broad Spectrum SPF 50

Active Ingredients

Avobenzone 3%

Homosalate 15%

Octisalate 5%

Purpose

Sunscreen

Uses

- helps prevent sunburn
- if used as directed with other sun protection measures (see Directions), decreses the risk of skin cancer and early skin aging caused by the sun

Warnings

For external use only

Do not useon damaged or broken skin

WHEN USING

When using this productkeep out of eyes. Rinse with water to remove.

Stop use and ask a doctorif rash occurs

Keep out of reach of children.If product is swallowed, get medical help or contact a Poison Control Center right away.

Directions

- apply liberally 15 minutes before sun exposure
- reapply
- after 80 minutes of swimming or sweating
- inmediately after towel drying
- at least every 2 hours
- Sun Protection Measures.Spending time in the sun increases your risk of skin cancer and early skin aging. To decrease this risk, regularly use a sunscreen with a Broad Spectrum SPF of 15 or higher and other sun protection measures, including:
- limit time in the sun, specially from 10 a.m. - 2 p.m.
- wear long-sleeve shirts, pants, hats & sunglasses.
- children under 6 months: Ask a doctor.

Inactive ingredients

Acrylic Acid/VP Crosspolymer, Aloe Barbadensis Leaf Juice, Butyrospermum Parkii (Shea) Butter, Caprylhydroxamic Acid, Caprylic/Capric Triglyceride, Daucus Carota Sativa (Carrot) Seed Oil, Ethyl Ferulate, Glycerin, Glyceryl Caprylate, Glyceryl Undecylenate, Helianthus Annuus (Sunflower) Seed Oil, Lavandula Angustifolia (Lavender) Oil, Olus Oil, Persea Gratissima (Avocado) Oil, Pongamia Pinnata Seed Extract, Simmondsia Chinensis (Jojoba) Seed Oil, Sodium Hydroxide, Tetrasodium Glutamate Diacetate , Tocopheryl Acetate, Triethoxycaprylylsilane, VP/Acrylates/Lauryl Methacrylate Copolymer, Water

Other Information

- protect this product from excessive heat and direct sun